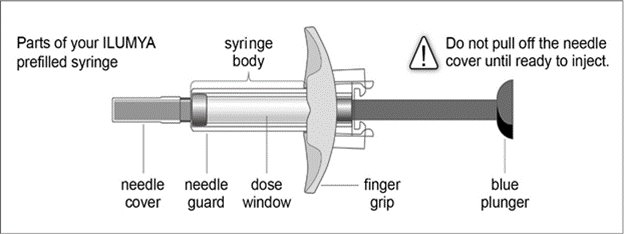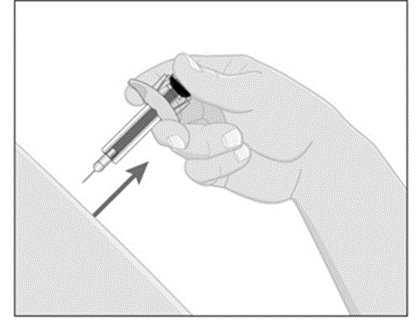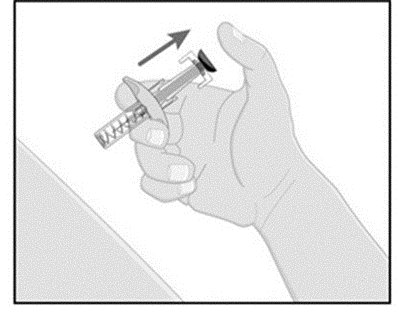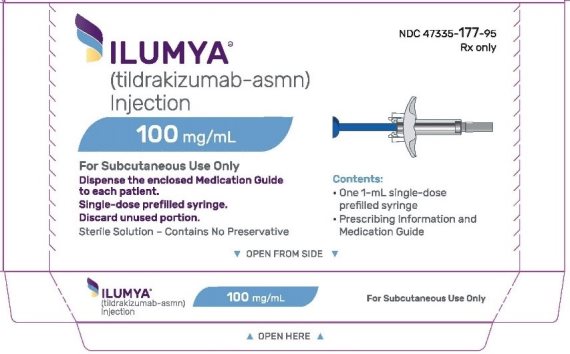 DRUG LABEL: ILUMYA
NDC: 47335-177 | Form: INJECTION, SOLUTION
Manufacturer: Sun Pharmaceutical Industries, Inc.
Category: prescription | Type: HUMAN PRESCRIPTION DRUG LABEL
Date: 20251225

ACTIVE INGREDIENTS: TILDRAKIZUMAB 100 mg/1 mL
INACTIVE INGREDIENTS: HISTIDINE 0.495 mg/1 mL; HISTIDINE MONOHYDROCHLORIDE 1.42 mg/1 mL; POLYSORBATE 80 0.5 mL/1 mL; SUCROSE 70 mg/1 mL; WATER 1 mL/1 mL

HIGHLIGHTS OF PRESCRIBING INFORMATION

These highlights do not include all the information needed to use ILUMYA safely and effectively. See full prescribing information for ILUMYA.
ILUMYA® (tildrakizumab-asmn) injection, for subcutaneous use Initial U.S. Approval: 2018

1 INDICATIONS AND USAGE

ILUMYA is an interleukin-23 antagonist indicated for the treatment of adults with moderate-to-severe plaque psoriasis who are candidates for systemic therapy or phototherapy. (1)

2 DOSAGE AND ADMINISTRATION

- See the full prescribing information for recommended evaluations and immunizations prior to treatment. (2.1)
- Administer by subcutaneous injection. (2.2)
- Recommended dosage is 100 mg at Weeks 0, 4, and every 12 weeks thereafter. (2.2)

3 DOSAGE FORMS AND STRENGTHS

Injection: 100 mg/mL solution in a single-dose prefilled syringe. (3)

4 CONTRAINDICATIONS

Serious hypersensitivity reaction to tildrakizumab or to any of the excipients. (4)

5 WARNINGS AND PRECAUTIONS

- Hypersensitivity: If a serious allergic reaction occurs, discontinue ILUMYA immediately and initiate appropriate therapy. (5.1)
- Infections: ILUMYA may increase the risk of infection. Instruct patients to seek medical advice if signs or symptoms of clinically important chronic or acute infection occur. If a serious infection develops, consider discontinuing ILUMYA until the infection resolves. (5.2)
- Pretreatment Evaluation for Tuberculosis (TB): Evaluate for TB prior to initiating treatment. (5.3)
- Immunizations: Avoid use of live vaccines. (5.4)

6 ADVERSE REACTIONS

Most common (≥1%) adverse reactions associated with ILUMYA treatment are upper respiratory infections, injection site reactions, and diarrhea. (6.1)

To report SUSPECTED ADVERSE REACTIONS, contact Sun Pharmaceutical Industries, Inc. at 1-800-818-4555 or FDA at 1-800-FDA-1088 or www.fda.gov/medwatch.

FULL PRESCRIBING INFORMATION

1 INDICATIONS AND USAGE

ILUMYA® is indicated for the treatment of adults with moderate-to-severe plaque psoriasis who are candidates for systemic therapy or phototherapy.

2 DOSAGE AND ADMINISTRATION

2.1 Recommended Evaluation and Immunization Prior to Treatment Initiation

- Evaluate patients for tuberculosis (TB) infection prior to initiating treatment with ILUMYA [see Warnings and Precautions (5.3)].
- Consider completion of all age appropriate immunizations according to current immunization guidelines. [see Warnings and Precautions (5.4)]

2.2 Dosage

ILUMYA is administered by subcutaneous injection. The recommended dosage is 100 mg at Weeks 0, 4, and every 12 weeks thereafter. Each syringe contains 1 mL of 100 mg/mL tildrakizumab-asmn.

2.3 Important Administration Instructions

ILUMYA should only be administered by a healthcare provider. Administer ILUMYA subcutaneously. Each prefilled syringe is for single-dose only. Inject the full amount (1 mL), which provides 100 mg of tildrakizumab per syringe. If a dose is missed, administer the dose as soon as possible. Thereafter, resume dosing at the regularly scheduled interval.

2.4 Preparation and Administration of ILUMYA

Before injection, remove ILUMYA carton from the refrigerator, and let the prefilled syringe (in the ILUMYA carton with the lid closed) sit at room temperature for 30 minutes.

Follow the instructions on the ILUMYA carton to remove the prefilled syringe correctly, and remove only when ready to inject. Do not pull off the needle cover until you are ready to inject.

Inspect ILUMYA visually for particulate matter and discoloration prior to administration. ILUMYA is a clear to slightly opalescent, colorless to slightly yellow solution. Do not use if the liquid contains visible particles or the syringe is damaged. Air bubbles may be present; there is no need to remove them.

Choose an injection site with clear skin and easy access (such as abdomen, thighs, or upper arm). Do not administer 2 inches around the navel or where the skin is tender, bruised, erythematous, indurated, or affected by psoriasis. Also, do not inject into scars, stretch marks, or blood vessels.

- While holding the body of the syringe, pull the needle cover straight off (do not twist) and discard.
- Inject ILUMYA subcutaneously as recommended [see Dosage and Administration (2.3)].
- Press down the blue plunger until it can go no further. This activates the safety mechanism that will ensure full retraction of the needle after the injection is given.
- Remove the needle from the skin entirely before letting go of the blue plunger. After the blue plunger is released, the safety lock will draw the needle inside the needle guard.

- Discard any unused portion. Dispose of used syringe.

3 DOSAGE FORMS AND STRENGTHS

Injection: 100 mg/mL solution in a single-dose prefilled syringe. ILUMYA is a clear to slightly opalescent, colorless to slightly yellow solution.

4 CONTRAINDICATIONS

ILUMYA is contraindicated in patients with a previous serious hypersensitivity reaction to tildrakizumab or to any of the excipients [see Warnings and Precautions (5.1)].

5 WARNINGS AND PRECAUTIONS

5.1 Hypersensitivity

Cases of angioedema and urticaria occurred in ILUMYA treated subjects in clinical trials. If a serious hypersensitivity reaction occurs, discontinue ILUMYA immediately and initiate appropriate therapy [see Adverse Reactions (6.1)].

5.2 Infections

ILUMYA may increase the risk of infection. Although infections were more common in the ILUMYA group (23%), the difference in frequency of infections between the ILUMYA group and the placebo group (22%) was less than 1% during the placebo-controlled period. However, subjects with active infections or a history of recurrent infections were not included in clinical trials. Upper respiratory infections occurred more frequently in the ILUMYA group than in the placebo group [see Adverse Reactions (6.1)].

The rates of serious infections for the ILUMYA group and the placebo group were ≤0.3%. Treatment with ILUMYA should not be initiated in patients with any clinically important active infection until the infection resolves or is adequately treated.

In patients with a chronic infection or a history of recurrent infection, consider the risks and benefits prior to prescribing ILUMYA. Instruct patients to seek medical help if signs or symptoms of clinically important chronic or acute infection occur. If a patient develops a clinically important or serious infection or is not responding to standard therapy, monitor the patient closely and consider discontinuation of ILUMYA until the infection resolves [see Adverse Reactions (6.1)].

5.3 Pretreatment Evaluation for Tuberculosis

Evaluate patients for tuberculosis (TB) infection prior to initiating treatment with ILUMYA. Initiate treatment of latent TB prior to administering ILUMYA. In clinical trials, of 55 subjects with latent TB who were concurrently treated with ILUMYA and appropriate TB prophylaxis, no subjects developed active TB (during the mean follow-up of 56.5 weeks). One other subject developed TB while receiving ILUMYA. Monitor patients for signs and symptoms of active TB during and after ILUMYA treatment. Consider anti-TB therapy prior to initiation of ILUMYA in patients with a past history of latent or active TB in whom an adequate course of treatment cannot be confirmed. Do not administer ILUMYA to patients with active TB infection.

5.4 Immunizations

Prior to initiating therapy with ILUMYA, consider completion of all age appropriate immunizations according to current immunization guidelines. Avoid the use of live vaccines in patients treated with ILUMYA. No data are available on the response to live or inactive vaccines.

6 ADVERSE REACTIONS

The following serious adverse reactions are discussed elsewhere in the labeling:

- Hypersensitivity Reactions [see Warnings and Precautions (5.1)]
- Infections [see Warnings and Precautions (5.2)]

6.1 Clinical Trials Experience

Because clinical trials are conducted under widely varying conditions, adverse reaction rates observed in the clinical trials of a drug cannot be directly compared to rates in the clinical trials of another drug and may not reflect the rates observed in practice.

Plaque Psoriasis

In clinical trials, a total of 1994 subjects with plaque psoriasis were treated with ILUMYA, of which 1083 subjects were treated with ILUMYA 100 mg. Of these, 672 subjects were exposed for at least 12 months, 587 for 18 months, and 469 for 24 months.

Data from three placebo-controlled trials (Trials 1, 2, and 3) in 705 subjects (mean age 46 years, 71% males, 81% white) were pooled to evaluate the safety of ILUMYA (100 mg administered subcutaneously at Weeks 0 and 4, followed by every 12 weeks [Q12W]) [see Clinical Studies (14)].

Placebo-Controlled Period (Weeks 0-16 of Trial 1 and Weeks 0-12 of Trials 2 and 3)

Table 1 summarizes the adverse reactions that occurred at a rate of at least 1% and at a higher rate in the ILUMYA group than in the placebo group.

Table 1: Adverse Reactions Occurring in ≥1% of Subjects in the ILUMYA Group and More Frequently than in the Placebo Group in the Plaque Psoriasis Trials 1, 2, and 3
Adverse Reaction | ILUMYA; 100 mg; (N=705); N (%) | Placebo; (N=355); N (%)
Upper respiratory infections* | 98 (14) | 41 (12)
Injection site reactions† | 24 (3) | 7 (2)
Diarrhea | 13 (2) | 5 (1)
* Upper respiratory infections include nasopharyngitis, upper respiratory tract infection, viral upper respiratory tract infection, and pharyngitis.
†Injection site reactions include injection site urticaria, pruritus, pain, reaction, erythema, inflammation, edema, swelling, bruising, hematoma, and hemorrhage.

During the placebo-controlled period of Trials 1, 2, and 3, adverse reactions that occurred at rates less than 1% but greater than 0.1% in the ILUMYA group and at a higher rate than in the placebo group included dizziness and pain in extremity.

Cases of angioedema and urticaria were reported in ILUMYA-treated subjects in clinical trials.

Safety through Week 52/64

Through Week 52 (Trials 1 and 3) and Week 64 (Trial 2), no new adverse reactions were identified with ILUMYA use and the frequency of the adverse reactions was similar to that observed during the placebo-controlled period.

Psoriasis of the Scalp

The safety of ILUMYA was assessed in a multicenter, randomized, double-blind, placebo-controlled trial (Trial 4) in 231 subjects with psoriasis of the scalp [see Clinical Studies (14)]. No new safety signals were identified through follow-up to Week 72.

Psoriasis of the Nail

The safety of ILUMYA was assessed in a multicenter, randomized, double-blind, placebo-controlled trial (Trial 5) in 99 subjects with psoriasis of the nail [see Clinical Studies (14)]. No new safety signals were identified through Week 28.

6.2 Immunogenicity

The observed incidence of anti-drug antibodies is highly dependent on the sensitivity and specificity of the assay. Differences in assay methods preclude meaningful comparisons of the incidence of anti-drug antibodies in the studies described below with the incidence of anti-drug antibodies in other studies.

Up to Week 64, approximately 6.5% of subjects treated with ILUMYA 100 mg developed antibodies to tildrakizumab. Of the subjects who developed antibodies to tildrakizumab, approximately 40% (2.5% of all subjects receiving ILUMYA) had antibodies that were classified as neutralizing. Development of neutralizing antibodies to tildrakizumab was associated with lower serum tildrakizumab concentrations and reduced efficacy.

8 USE IN SPECIFIC POPULATIONS

8.1 Pregnancy

Pregnancy Exposure Registry

There is a pregnancy exposure registry that monitors outcomes in women with plaque psoriasis who become pregnant while being treated with or who are exposed to ILUMYA during pregnancy. These patients should be encouraged to enroll in this registry by calling MotherToBaby a service of the Organization of Teratology Information Specialists (OTIS) at 1-866-626-6847 or by visiting the website https://mothertobaby.org/ongoing-study/ilumya-tildrakizumab-asmn.

Risk Summary

Limited available data with ILUMYA use in pregnant women are insufficient to inform a drug associated risk of adverse developmental outcomes. Monoclonal antibodies are actively transported across the placenta (see Clinical Considerations). An embryofetal developmental study conducted with tildrakizumab in pregnant monkeys revealed no treatment-related effects to the developing fetus when tildrakizumab was administered subcutaneously during organogenesis to near parturition at doses up to 159 times the maximum recommended human dose (MRHD). When dosing was continued until parturition, an increase in neonatal death was observed at 59 times the MRHD [see Data below]. The clinical significance of this nonclinical finding is unknown.

All pregnancies have a background risk of birth defect, loss, or other adverse outcomes. The background risk of major birth defects and miscarriage for the indicated population is unknown. In the U.S. general population, the estimated background risk of major birth defects and miscarriage in clinically recognized pregnancies is 2-4% and 15-20%, respectively.

Clinical Considerations

Fetal/Neonatal Adverse Reactions

Transport of endogenous IgG antibodies across the placenta increases as pregnancy progresses, and peaks during the third trimester. Therefore, ILUMYA may be present in infants exposed in utero. The potential clinical impact of tildrakizumab exposure in infants exposed in utero should be considered.

Data

Animal Data

In an embryofetal developmental study, subcutaneous doses up to 300 mg/kg tildrakizumab were administered to pregnant cynomolgus monkeys once every two weeks during organogenesis to gestation day 118 (22 days from parturition). No maternal or embryofetal toxicities were observed at doses up to 300 mg/kg (159 times the MRHD of 100 mg, based on AUC comparison). Tildrakizumab crossed the placenta in monkeys.

In a pre- and postnatal developmental study, subcutaneous doses up to 100 mg/kg tildrakizumab were administered to pregnant cynomolgus monkeys once every two weeks from gestation day 50 to parturition. Neonatal deaths occurred in the offspring of one control monkey, two monkeys at 10 mg/kg dose (6 times the MRHD based on AUC comparison), and four monkeys at 100 mg/kg dose (59 times the MRHD based on AUC comparison). The clinical significance of these nonclinical findings is unknown. No tildrakizumab-related adverse effects were noted in the remaining infants from birth through 6 months of age.

8.2 Lactation

Risk Summary

There are no data on the presence of tildrakizumab in human milk, the effects on the breastfed infant, or the effects on milk production. Human IgG is known to be present in human milk. Tildrakizumab was detected in the milk of monkeys [see Data].

The developmental and health benefits of breastfeeding should be considered along with the mother’s clinical need for ILUMYA and any potential adverse effects on the breastfed child from ILUMYA or from the underlying maternal condition.

Data

Animal Data

Tildrakizumab was detected in breast milk of monkeys in the pre- and postnatal developmental study described in 8.1. The mean tildrakizumab concentrations in milk were approximately 0.09 – 0.2% of that in serum on postpartum days 28 and 91.

8.4 Pediatric Use

Safety and effectiveness of ILUMYA in pediatric patients (<18 years of age) have not been established.

8.5 Geriatric Use

A total of 1083 subjects were exposed to ILUMYA 100 mg during Phase 2 and 3 trials. A total of 92 subjects were 65 years or older, and 17 subjects were 75 years or older. Although no differences in safety or efficacy were observed between older and younger subjects, the number of subjects aged 65 and over is not sufficient to determine whether they responded differently from younger subjects [see Clinical Pharmacology (12.3)].

10 OVERDOSAGE

In the event of overdosage, monitor the patient for any signs or symptoms of adverse reactions, administer appropriate symptomatic treatment immediately, and contact Poison Control at 1-800-222-1222.

11 DESCRIPTION

Tildrakizumab-asmn is a humanized IgG1/k antibody that specifically binds to the p19 subunit of interleukin-23 (IL-23).

Tildrakizumab-asmn is produced in a recombinant Chinese hamster ovary (CHO) cell line and has an approximate molecular mass of 147 kilodaltons.

ILUMYA (tildrakizumab-asmn) injection, for subcutaneous use, is a sterile, clear to slightly opalescent, colorless to slightly yellow solution. ILUMYA is supplied in a single-dose prefilled syringe with a glass barrel and 29-gauge fixed, 1/2-inch needle.

The syringe is fitted with a passive needle guard and a needle cover.

Each 1 mL single-dose prefilled syringe contains 100 mg of tildrakizumab-asmn formulated in: L-histidine (0.495 mg), L-histidine hydrochloride monohydrate (1.42 mg), polysorbate 80 (0.5 mg), sucrose (70.0 mg), and Water for Injection, USP with a pH of 5.7-6.3.

12 CLINICAL PHARMACOLOGY

12.1 Mechanism of Action

Tildrakizumab is a humanized IgG1/k monoclonal antibody that selectively binds to the p19 subunit of IL-23 and inhibits its interaction with the IL-23 receptor. IL-23 is a naturally occurring cytokine that is involved in inflammatory and immune responses. Tildrakizumab inhibits the release of proinflammatory cytokines and chemokines.

12.2 Pharmacodynamics

No formal pharmacodynamics studies have been conducted with ILUMYA.

12.3 Pharmacokinetics

Tildrakizumab pharmacokinetics increases proportionally over a dose range from 50 mg to 200 mg (0.5 to 2 times the approved recommended dosage) following subcutaneous administration in subjects with plaque psoriasis. Steady-state concentrations were achieved by Week 16 following subcutaneous administration of tildrakizumab at Weeks 0, 4, and every 12 weeks thereafter. At the 100 mg dose at Week 16, the mean (± SD) steady-state trough concentrations ranged from 1.22 ± 0.94 mcg/mL to 1.47 ± 1.12 mcg/mL. The geometric mean (CV%) steady-state Cmax was 8.1 mcg/mL (34%).

Absorption

The absolute bioavailability of tildrakizumab was estimated to be 73-80% following subcutaneous injection. The peak concentration (Cmax) was reached by approximately 6 days.

Distribution

The geometric mean (CV%) volume of distribution is 10.8 L (24%).

Elimination

The geometric mean (CV%) systemic clearance was 0.32 L/day (38%) and the half-life was approximately 23 days (23%).

Metabolism

The metabolic pathway of tildrakizumab has not been characterized. As a humanized IgG1/k monoclonal antibody, tildrakizumab is expected to be degraded into small peptides and amino acids via catabolic pathways in a manner similar to endogenous IgG.

Specific Populations

No clinically significant differences in the pharmacokinetics of tildrakizumab were observed based on age (≥18 years). No specific studies have been conducted to determine the effect of renal or hepatic impairment on the pharmacokinetics of tildrakizumab.

Body Weight

Tildrakizumab concentrations were lower in subjects with higher body weight.

Drug Interaction Studies

Cytochrome P450 Substrates

The AUCinf of dextromethorphan (CYP2D6 substrate) increased by 20% when used concomitantly with tildrakizumab 200 mg (two times the approved recommended dose) administered subcutaneously at Weeks 0 and 4 in subjects with plaque psoriasis. No clinically significant changes in AUCinf of caffeine (CYP1A2 substrate), warfarin (CYP2C9 substrate), omeprazole (CYP2C19 substrate), and midazolam (CYP3A4 substrate) were observed.

13 NONCLINICAL TOXICOLOGY

13.1 Carcinogenesis, Mutagenesis, Impairment of Fertility

Animal studies have not been conducted to evaluate the carcinogenic or mutagenic potential of ILUMYA.

No effects on fertility parameters were observed in male or female cynomolgus monkeys that were administered tildrakizumab at subcutaneous or intravenous doses up to 140 mg/kg once every two weeks for 3 months (133 or 155 times the MRHD, respectively, based on AUC comparison). The monkeys were not mated to evaluate fertility.

14 CLINICAL STUDIES

Plaque Psoriasis

In two multicenter, randomized, double-blind, placebo-controlled trials (Trial 2 [NCT01722331] and Trial 3 [NCT01729754]), 926 subjects were treated with ILUMYA 100 mg (N=616) or placebo (N=310). Subjects had a Physician Global Assessment (PGA) score of ≥3 (moderate) on a 5-point scale of overall disease severity, Psoriasis Area and Severity Index (PASI) score ≥12, and a minimum body surface area (BSA) involvement of 10%. Subjects with guttate, erythrodermic, or pustular psoriasis were excluded.

In both trials, subjects were randomized to either placebo or ILUMYA (100 mg at Week 0, Week 4, and every twelve weeks thereafter [Q12W]) up to 64 weeks.

Trials 2 and 3 assessed the changes from baseline to Week 12 in the two co-primary endpoints:

- PASI 75, the proportion of subjects who achieved at least a 75% reduction in the PASI composite score.
- PGA of 0 (“cleared”) or 1 (“minimal”), the proportion of subjects with a PGA of 0 or 1 and at least a 2-point improvement.

Other evaluated outcomes in Trials 2 and 3 included the proportion of subjects who achieved a reduction from baseline in PASI score of at least 90% (PASI 90) and a reduction of 100% in PASI score (PASI 100) at Week 12 and maintenance of efficacy up to Week 64.

In both trials, subjects in the ILUMYA 100 mg and placebo treatment groups were predominantly men (69%) and White (80%), with a mean age of 46 years. At baseline, these subjects had a median affected BSA of 27%, a median PASI score of 17.8, and approximately 33% had a PGA score of 4 (“marked”) or 5 (“severe”). Approximately 34% had received prior phototherapy, 39% had received prior conventional systemic therapy, and 18% had received prior biologic therapy for the treatment of psoriasis. Approximately 16% of subjects had a history of psoriatic arthritis.

Clinical Response at Week 12

The results of Trials 2 and 3 are presented in Table 2.

Table 2: Efficacy Results at Week 12 in Adults with Plaque Psoriasis in Trials 2 and 3 (NRI*)
 | Trial 2 (NCT01722331) |  | Trial 3 (NCT01729754)
 | ILUMYA 100 mg; (N=309); n (%) | Placebo; (N=154); n (%) | ILUMYA 100 mg; (N=307); n (%) | Placebo; (N=156); n (%)
PGA of 0 or 1†,‡ | 179 (58) | 11 (7) | 168 (55) | 7 (4)
PASI 75† | 197 (64) | 9 (6) | 188 (61) | 9 (6)
PASI 90 | 107 (35) | 4 (3) | 119 (39) | 2 (1)
PASI 100 | 43 (14) | 2 (1) | 38 (12) | 0 (0)
* NRI = Non-Responder Imputation
† Co-Primary Endpoints
‡ PGA score of 0 (“cleared”) or 1 (“minimal”)

Examination of age, gender, race, and previous treatment with a biologic did not identify differences in response to ILUMYA among these subgroups at Week 12.

Maintenance of Response and Durability of Response

In Trial 2, subjects originally randomized to ILUMYA and who were responders at Week 28 (i.e., PASI 75) were re-randomized to an additional 36 weeks of either maintaining the same dose of ILUMYA Q12W (every twelve weeks) or placebo.

At Week 28, 229 (74%) subjects treated with ILUMYA 100 mg were PASI 75 responders. At Week 64, 84% of subjects who continued on ILUMYA 100 mg Q12W maintained PASI 75 compared to 22% of subjects who were re-randomized to placebo. In addition, for subjects who were re-randomized and also had a PGA score of 0 or 1 at Week 28, 69% of subjects who continued on ILUMYA 100 mg Q12W maintained this response (PGA 0 or 1) at Week 64 compared to 14% of subjects who were re-randomized to placebo.

For PASI 75 responders at Week 28 who were re-randomized to treatment withdrawal (i.e., placebo), the median time to loss of PASI 75 was approximately 20 weeks.

In addition, for subjects who were re-randomized to placebo and also had a PGA score of 0 or 1 at Week 28, the median time to loss of PGA score of 0 or 1 was approximately 16 weeks.

Psoriasis of the Scalp

In a multicenter, randomized, double-blind, placebo-controlled trial (Trial 4 [NCT03897088]) 231 subjects with moderate to severe psoriasis of the scalp (IGA Scalp score of 3 or 4) were treated subcutaneously with ILUMYA 100 mg (n=117) or placebo (n=114) at Weeks 0 and 4. Of the 231 randomized subjects, 217 subjects completed Part 1 (Day 1 to Week 16). In Part 2 of the trial, subjects previously randomized to placebo were switched to ILUMYA 100 mg at Weeks 16, 20, 32, and 44, and those in the ILUMYA 100 mg arm continued to receive ILUMYA 100 mg at Weeks 16, 28, 40, and 52.

The trial population was 79% White, 8% Black or African American, 6% Asian, 3% Native Hawaiian or Other Pacific Islander, 2% American Indian or Alaska Native, and 2% Other; for ethnicity, 65% of subjects identified as Not Hispanic or Latino. The trial population was 60% male and the mean age was 45 years. At baseline, these subjects had a median affected scalp surface area of 50%, a median PASI score of 16.7, and IGA Scalp score of 3 (“moderate”) or 4 (“severe”) in 81% and 16%, respectively.

The primary endpoint was the proportion of subjects with IGA Scalp score of “clear” and “almost clear” with at least 2-point reduction from Baseline at Week 16.

Other evaluated outcomes included the proportion of subjects achieving a) Psoriasis Scalp Severity Index (PSSI) 90 (≥90% improvement from Baseline in PSSI) at Week 16; b) PSSI 90 at Week 12; and c) IGA Scalp score of “clear” or “almost clear” with at least 2-point reduction from Baseline at Week 12.

The efficacy results from Trial 4 are presented in Table 3.

Table 3: Efficacy Results for Primary and Secondary Endpoints in Subjects with Moderate to Severe Psoriasis of the Scalp in Trial 4 (mITT, NRI*)
 | Trial 4 (NCT03897088)
 | ILUMYA 100 mg; (N=89); n (%) | Placebo; (N=82); n (%)
Primary Endpoint
IGA Scalp Response Rate for score 0 or 1 (clear or almost clear) at Week 16 with at least 2-point reduction from baseline score | 44 (49) | 6 (7)
Secondary Endpoints
PSSI 90 Response Rate at Week 16 | 54 (61) | 4 (5)
IGA Scalp Response Rate for score 0 or 1 (clear or almost clear) at Week 12 with at least 2-point reduction from baseline score | 41 (46) | 4 (5)
PSSI 90 Response Rate at Week 12 | 43 (48) | 2 (2)
Note: IGA = Investigator Global Assessment. PSSI = psoriasis scalp severity index.
* NRI = Non-responder imputation; mITT = modified Intent-to-treat, all randomized subjects, excluding subjects enrolled early in the trial evaluated under a different IGA Scalp scale.

Psoriasis of the Nail

In a randomized, multicenter, double-blind, placebo-controlled trial (Trial 5 [NCT03897075]), 99 subjects with moderate to severe psoriasis of the nail received subcutaneous ILUMYA 100 mg (N=51) or placebo (N=48) at Weeks 0, 4, and 16. Of the 99 randomized subjects, 78 subjects completed Part 1 (Day 1 to Week 28) of the trial.

The trial population was 79% White, 2% Black or African American, 15% Asian and 4% Other; for ethnicity, 62% of subjects identified as Not Hispanic or Latino. The trial population was 71% male and the mean age was 46 years. At baseline, these subjects had a median Modified Nail Psoriasis Severity Index (mNAPSI) score of 34 and a median PASI score of 16.

The primary endpoint was the proportion of subjects who achieved at least a 75% improvement from baseline in total mNAPSI at Week 28.

The efficacy results from Trial 5 are presented in Table 4.

TABLE 4: Efficacy Results for the Modified Nail Psoriasis Severity Index in Subjects with Moderate to Severe Psoriasis of the Nail in Trial 5 (ITT, NRI*)
 | Trial 5
 | ILUMYA 100mg; N=51; n (%) | Placebo; N=48; n (%)
Proportion of subjects who achieve at least a 75% improvement from baseline in total mNAPSI at Week 28 | 13 (26) | 2 (4)
ITT = Intent to Treat.
mNAPSI = modified Nail Psoriasis Severity Index
* NRI = Non-responder Imputation

16 HOW SUPPLIED/STORAGE AND HANDLING

How Supplied

ILUMYA (tildrakizumab-asmn) Injection is a sterile, preservative-free, clear to slightly opalescent, colorless to slightly yellow solution. ILUMYA is supplied as one single-dose prefilled syringe per carton that delivers 1 mL of a 100 mg/mL solution.

- NDC 47335-177-95

Each prefilled syringe is equipped with a passive needle guard and a needle cover.

Storage and Handling

Store refrigerated at 2°C to 8°C (36°F to 46°F) in the original carton to protect from light until the time of use. Do not freeze. Do not shake. ILUMYA can be kept at room temperature at 25°C (77°F) for up to 30 days in the original carton to protect from light. Once stored at room temperature, do not place back in the refrigerator. If not used within 30 days, discard ILUMYA. Do not store ILUMYA above 25°C (77°F).

17 PATIENT COUNSELING INFORMATION

Advise the patient and/or caregiver to read the FDA-approved patient labeling (Medication Guide).

Instruct patients and/or caregivers to read the Medication Guide before starting ILUMYA therapy and to reread the Medication Guide each time the prescription is renewed. Advise patients of the potential benefits and risks of ILUMYA.

Hypersensitivity

Advise patients to seek immediate medical attention if they experience any symptoms of serious hypersensitivity reactions [see Warnings and Precautions (5.1)].

Infections

Instruct patients of the importance of communicating any history of infections to the doctor and contacting their doctor if they develop any symptoms of infection [see Warnings and Precautions (5.2)].

Immunizations

Instruct patients to inform the healthcare practitioner that they are taking ILUMYA prior to a potential vaccination since the use of live vaccine is not recommended [see Warnings and Precautions (5.4)].

Pregnancy

Advise patients that there is a pregnancy registry that monitors pregnancy outcomes in women exposed to ILUMYA during pregnancy [see Use in Specific Populations, Pregnancy (8.1)].

Manufactured by: Sun Pharmaceutical Industries Limited

Mumbai, Maharashtra India 400 063

U.S. License No. 2092
U.S. Patent No. 8,404,813; 8,293,883 and 9,809,648
Tildrakizumab-asmn (active ingred.) Product of South Korea.

Distributed by: Sun Pharmaceutical Industries, Inc.
Cranbury, NJ 08512

ILUMYA is a registered trademark of Sun Pharmaceutical Industries Limited

©2025 Sun Pharmaceutical Industries Limited

All rights reserved

Rev. DEC 2025

10009296-08

Medication Guide

ILUMYA® (e-LOOM-me-a)

(tildrakizumab-asmn)

injection, for subcutaneous use

What is the most important information I should know about ILUMYA?

ILUMYA may cause serious side effects, including:

Serious allergic reactions. Get emergency medical help right away if you get any of the following symptoms of a serious allergic reaction:

- feel faint
- swelling of your face, eyelids, lips, mouth, tongue or throat
- skin rash

- trouble breathing or throat tightness
- chest tightness

Infections. ILUMYA is a medicine that may lower the ability of your immune system to fight infections and may increase your risk of infections. Your healthcare provider should check you for infections and tuberculosis (TB) before starting treatment with ILUMYA and may treat you for TB before you begin treatment with ILUMYA if you have a history of TB or have active TB. Your healthcare provider should watch you closely for signs and symptoms of TB during and after treatment with ILUMYA.

Tell your healthcare provider right away if you have an infection or have symptoms of an infection, including:

- fever, sweats, or chills
- cough
- shortness of breath
- blood in your phlegm (mucus)

- muscle aches
- warm, red, or painful skin or sores on your body different from your psoriasis

- weight loss
- diarrhea or stomach pain
- burning when you urinate or urinating more often than normal

See “What are the possible side effects of ILUMYA?” for more information about side effects.

What is ILUMYA?

ILUMYA is a prescription medicine used to treat adults with moderate to severe plaque psoriasis who may benefit from taking injections, pills (systemic therapy) or treatment using ultraviolet or UV light (phototherapy).

It is not known if ILUMYA is safe and effective in children under 18 years of age.

Do not use ILUMYA if you have had a severe allergic reaction to tildrakizumab or any of the other ingredients in ILUMYA. See the end of this Medication Guide for a complete list of ingredients in ILUMYA.

Before receiving ILUMYA, tell your healthcare provider about all of your medical conditions, including if you:

- have any of the conditions or symptoms listed in the section “What is the most important information I should know about ILUMYA?”
- have an infection that does not go away or that keeps coming back
- have TB or have been in close contact with someone with TB
- recently received or are scheduled to receive a vaccine (immunization). You should avoid receiving live vaccines during treatment with ILUMYA.
- are pregnant or plan to become pregnant. It is not known if ILUMYA can harm your unborn baby.
  - If you become pregnant during treatment with ILUMYA, you are encouraged to enroll in the pregnancy registry. The purpose of this registry is to collect information about the health of you and your baby. Talk with your healthcare provider or call 1-866-626-6847 to enroll in this registry or visit https://mothertobaby.org/ongoing-study/ilumya-tildrakizumab-asmn.
- are breastfeeding or plan to breastfeed. It is not known if ILUMYA passes into your breast milk. Tell your healthcare provider about all the medicines you take, including prescription and over-the-counter medicines, vitamins, and herbal supplements.

How will I receive ILUMYA?

- ILUMYA should only be given to you by a healthcare provider.
- ILUMYA is given as an injection under your skin (subcutaneous injection) in areas of your body such as your thighs, stomach area (abdomen), or upper arm.
- If you miss a follow-up appointment and do not receive your dose of ILUMYA, schedule another appointment as soon as possible.

What are the possible side effects of ILUMYA?

ILUMYA may cause serious side effects. See “What is the most important information I should know about ILUMYA?”

The most common side effects of ILUMYA include:

- upper respiratory infections

- injection site reactions

- diarrhea

These are not all of the possible side effects of ILUMYA. Call your doctor for medical advice about side effects. You may report side effects to FDA at 1-800-FDA-1088.

General information about the safe and effective use of ILUMYA.

Medicines are sometimes prescribed for purposes other than those listed in a Medication Guide. You can ask your healthcare provider for information about ILUMYA that is written for health professionals.

What are the ingredients in ILUMYA?

Active ingredient: tildrakizumab-asmn

Inactive ingredients: L-histidine, L-histidine hydrochloride monohydrate, polysorbate 80, sucrose, and Water for Injection, USP.

Manufactured by: Sun Pharmaceutical Industries Limited

Mumbai, Maharashtra India 400 063
U.S. License No. 2092
U.S. Patent No. 8,404,813; 8,293,883 and 9,809,648
Tildrakizumab-asmn (active ingred.) Product of South Korea.

Distributed by:

Sun Pharmaceutical Industries, Inc.
Cranbury, NJ 08512

ILUMYA is a registered trademark of Sun Pharmaceutical Industries Limited
© 2025 Sun Pharmaceutical Industries Limited
All rights reserved

This Medication Guide has been approved by the U.S. Food and Drug Administration.

Revised: 12/2025

Package/Label Display Panel

NDC 47335-177-95
Rx only

ILUMYA®
tildrakizumab-asmn injection

100 mg/mL

For Subcutaneous Use Only
Dispense the enclosed Medication Guide to each patient.
Single-dose prefilled syringe.
Discard unused portion.

Sterile Solution - Contains No Preservative

Sun Pharmaceutical Industries, Inc.